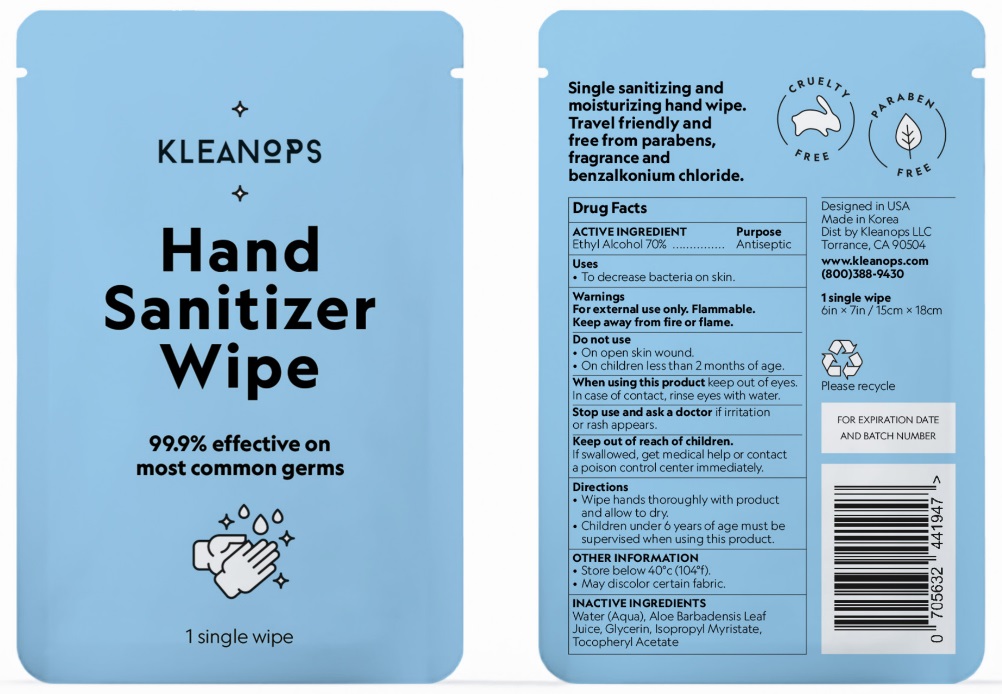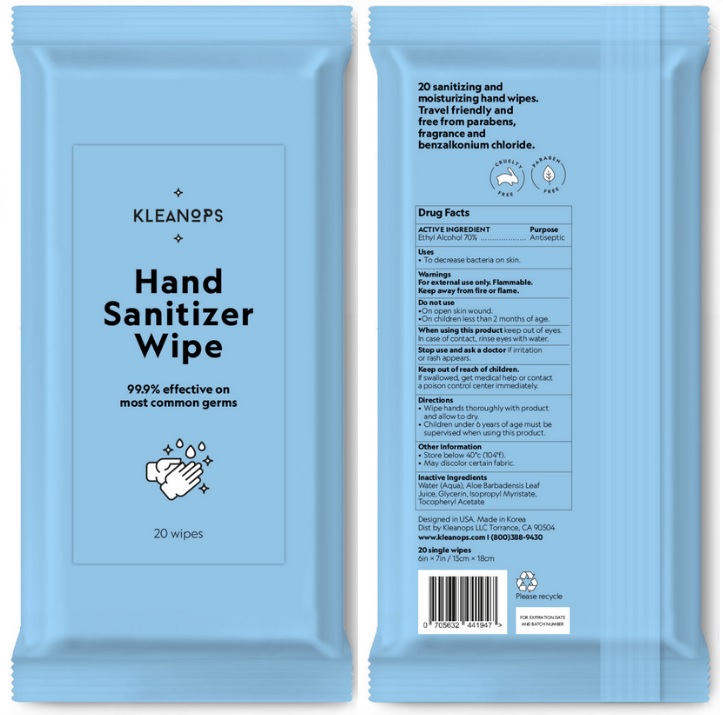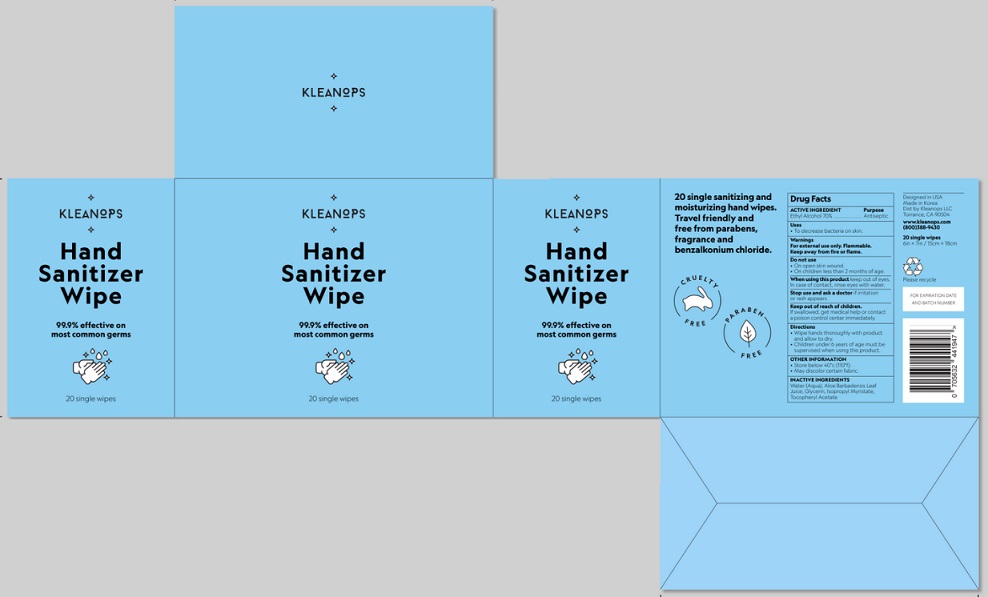 DRUG LABEL: Kleanops
NDC: 79912-001 | Form: CLOTH
Manufacturer: KLEANOPS LLC
Category: otc | Type: HUMAN OTC DRUG LABEL
Date: 20211021

ACTIVE INGREDIENTS: ALCOHOL 70 mL/100 mL
INACTIVE INGREDIENTS: WATER; ALOE VERA LEAF; GLYCERIN; ISOPROPYL MYRISTATE; .ALPHA.-TOCOPHEROL ACETATE

Active Ingredient

Ethyl Alcohol 70% v/v.

Purpose

Antiseptic

Uses

To decrease bacteria on skin.

Warnings

For external use only.

Flammable. Keep away from heat or flame.

Do not use
• On open skin wound.
• On children less than 2 months of age.

When using this product keep out of eyes. In case of contact, rinse eyes with water.

Stop use and ask a doctor if irritation or rash appears.

Keep out of reach of children. If swallowed, get medical help or contact a Poison Control Center immediately.

Directions

- Wipe hands thoroughly with product and allow to dry.
- Children under 6 years of age must be supervised when using this product.

OTHER INFORMATION

• Store below 40°C (104°F).
• May discolor certain fabric.

Inactive ingredients

Water (Aqua), Aloe Barbadensis Leaf Juice, Glycerin, Isopropyl Myristate, Tocopheryl Acetate